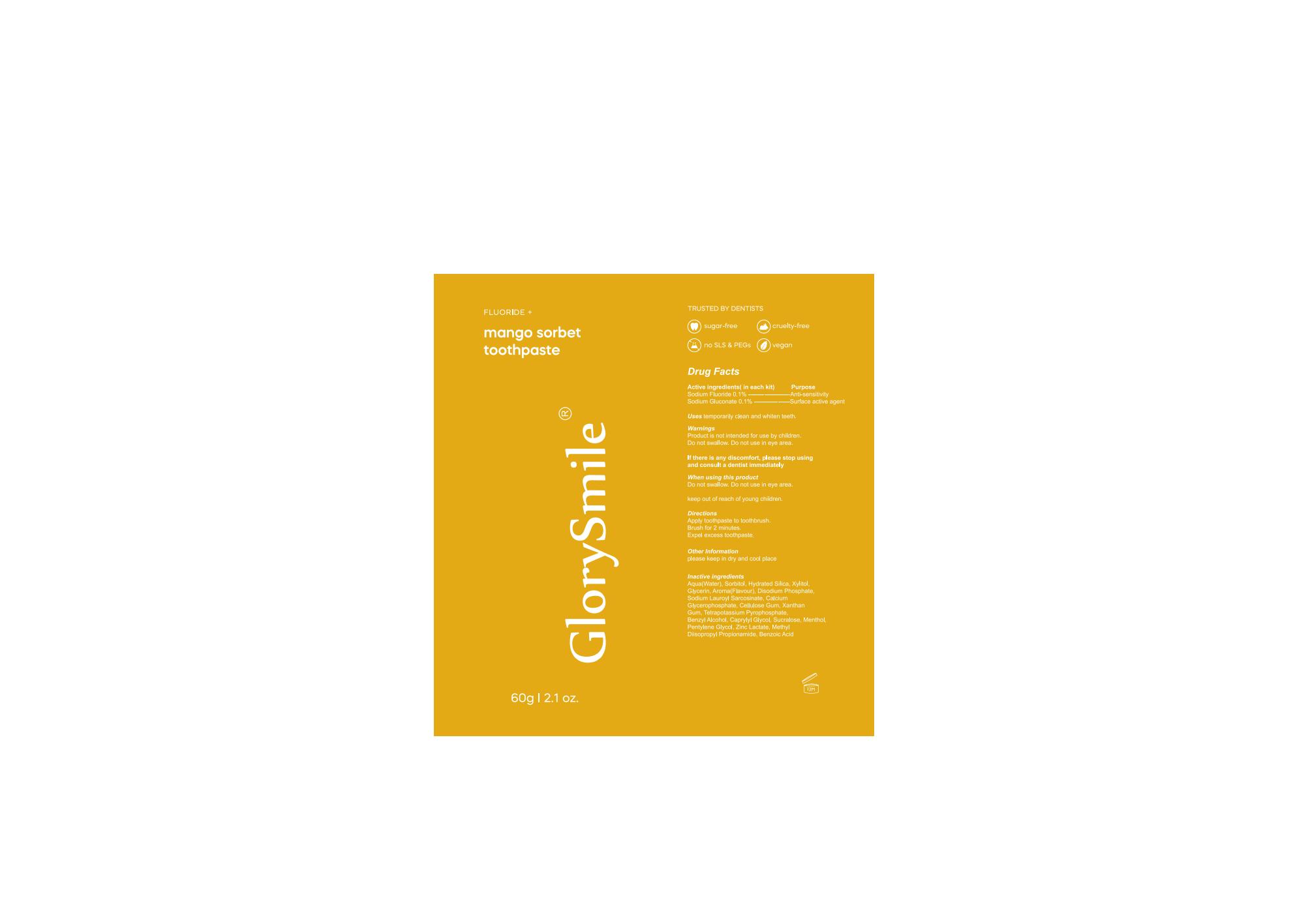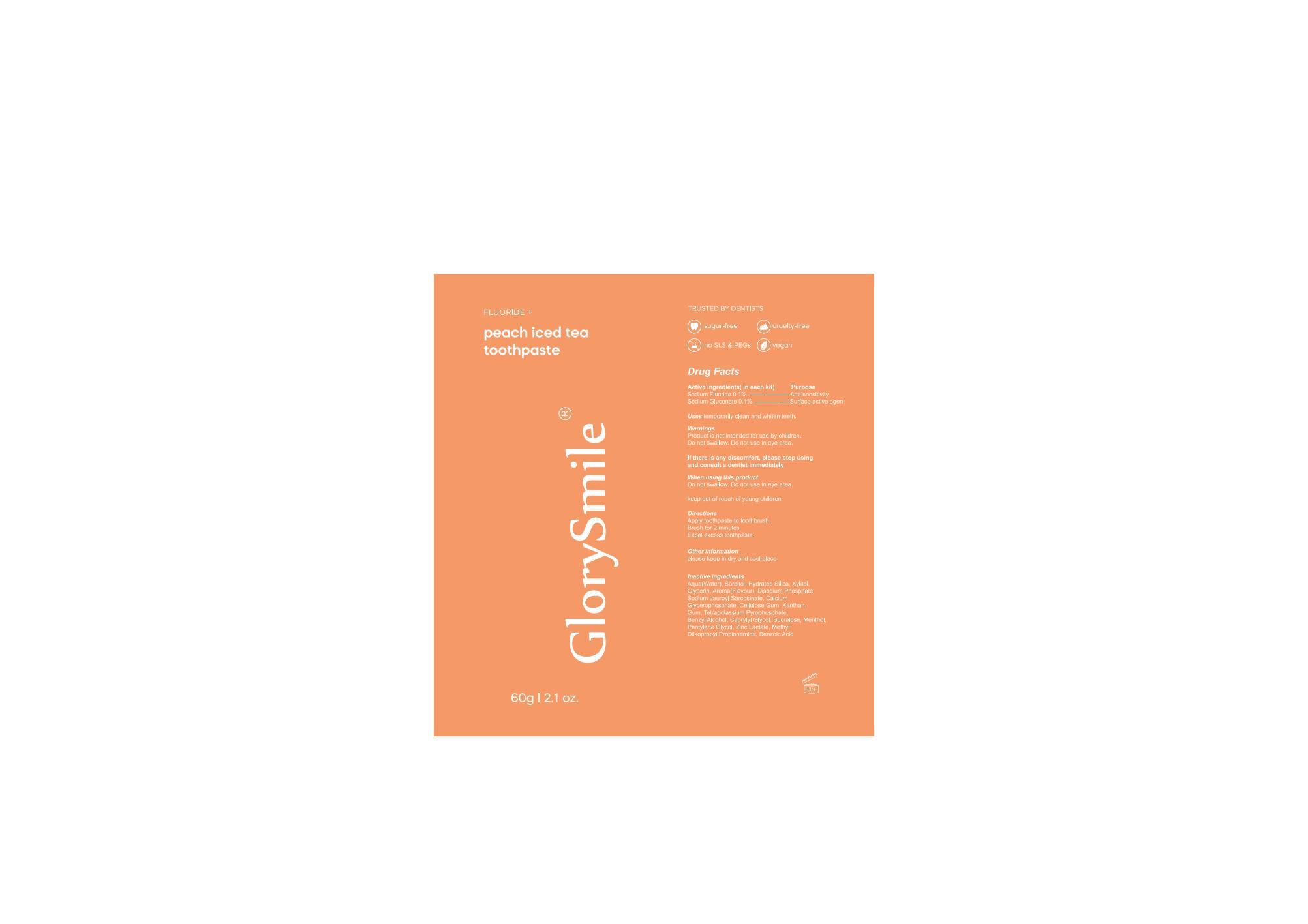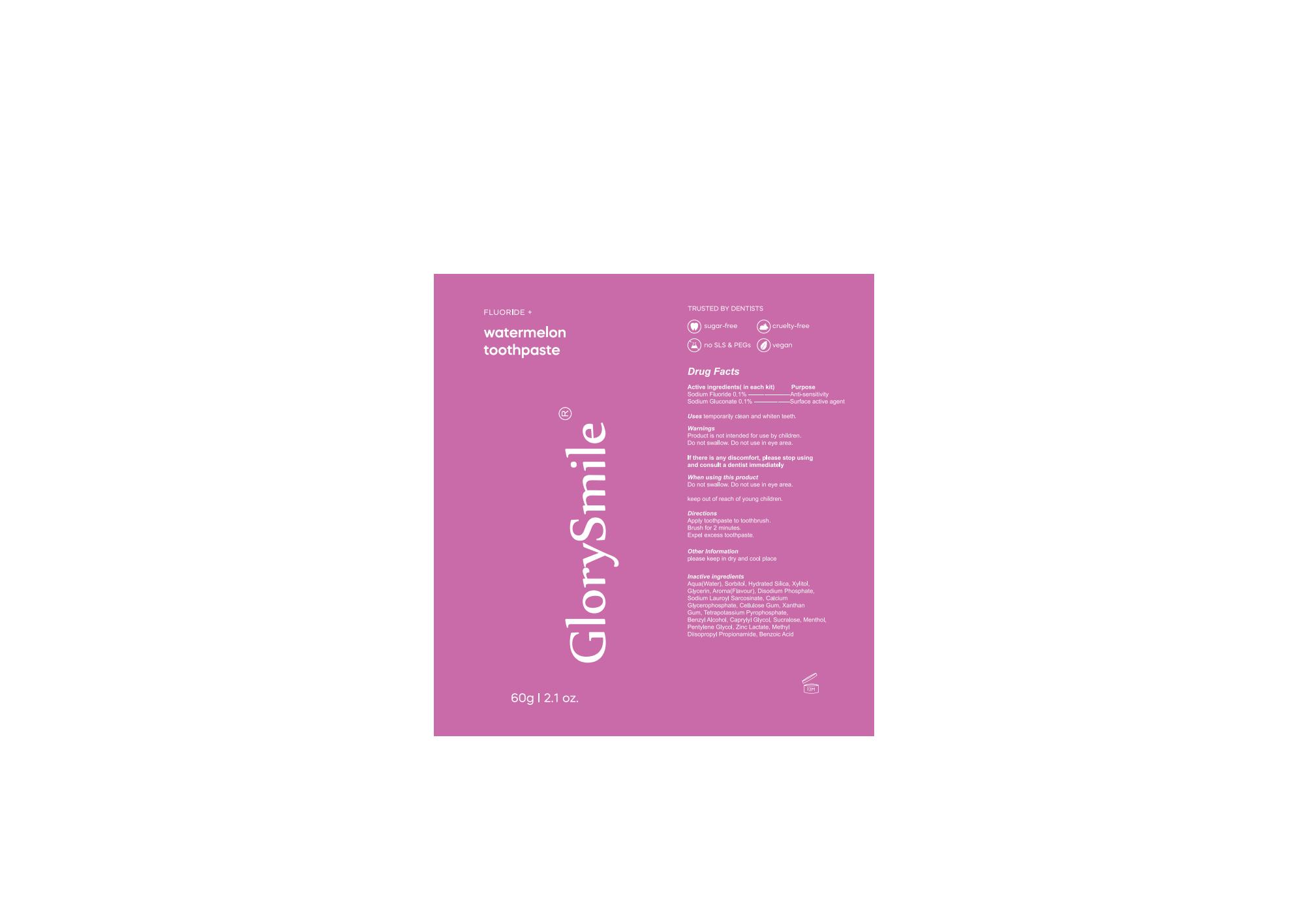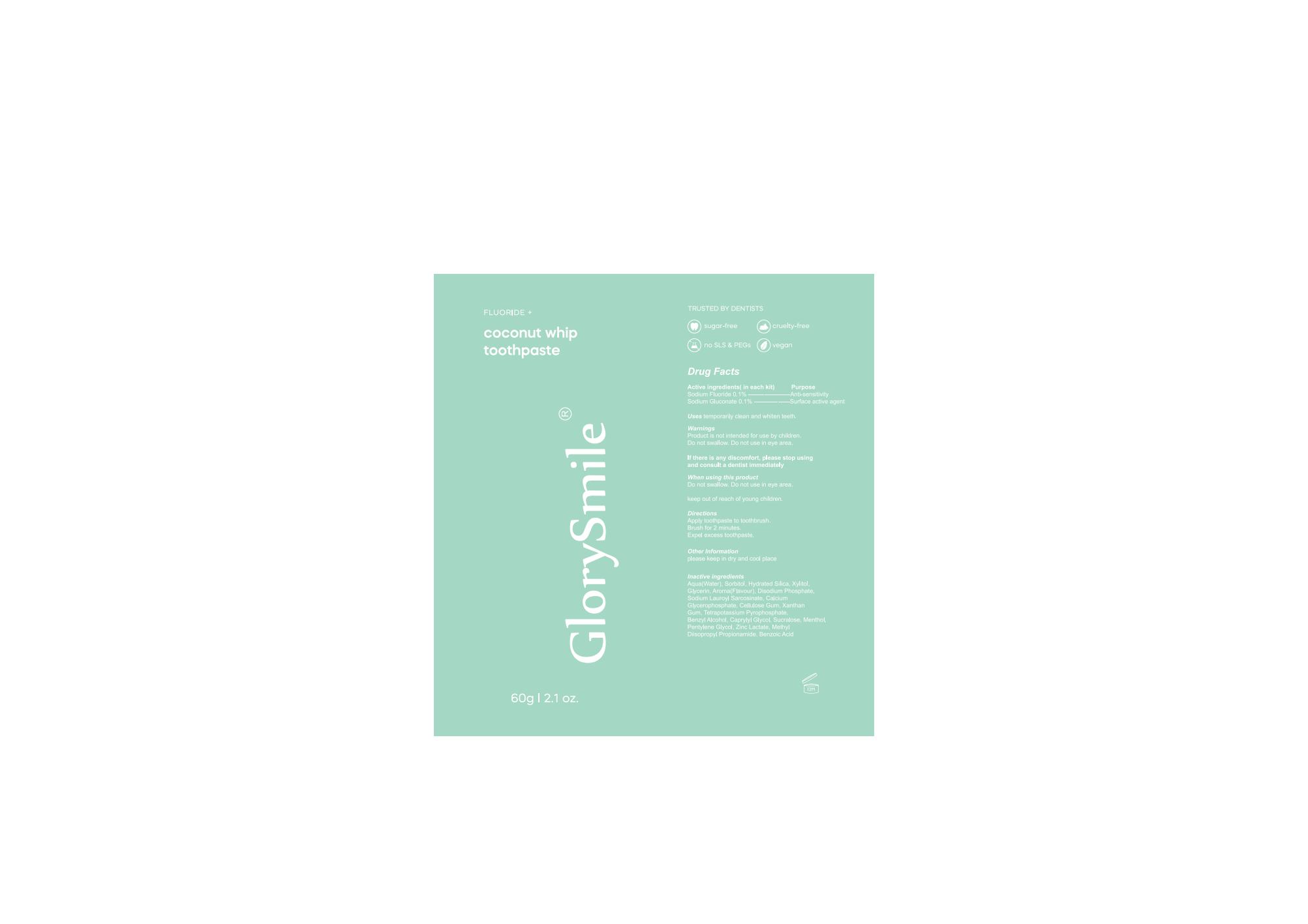 DRUG LABEL: Glorysmile Toothpaste.
NDC: 83778-005 | Form: CREAM
Manufacturer: Nanchang Dental Bright Technology Co.,Ltd.
Category: otc | Type: HUMAN OTC DRUG LABEL
Date: 20231129

ACTIVE INGREDIENTS: SODIUM FLUORIDE 0.1 g/100 g; SODIUM GLUCONATE 0.1 g/100 g
INACTIVE INGREDIENTS: FRAGRANCE CLEAN ORC0600327; SUCRALOSE; POTASSIUM PYROPHOSPHATE; CAPRYLYL GLYCOL; WATER; SORBITOL; HYDRATED SILICA; SODIUM PHOSPHATE, DIBASIC, ANHYDROUS; SODIUM LAUROYL SARCOSINATE; CARBOXYMETHYLCELLULOSE SODIUM, UNSPECIFIED FORM; XANTHAN GUM; BENZYL ALCOHOL; ZINC LACTATE; BENZOIC ACID; XYLITOL; GLYCERIN; CALCIUM GLYCEROPHOSPHATE; METHYL DIISOPROPYL PROPIONAMIDE; MENTHOL; PENTYLENE GLYCOL

Active Ingredient

Sodium Fluoride 0.1%

Sodium Gluconate 0.1%

Purpose

Teeth cleaning

Use

temporarily clean and whiten teeth.

Warnings

Product is not intended for use by children.
Do not swallow. Do not use in eye area.

When Using

Do not swallow. Do not use in eye area

keep out of reach of young children.

Directions

Apply toothpaste to toothbrush.

Brush for 2 minutes.

Expel excess toothpaste

Other Information

please keep in dry and cool place

Inactive ingredients

Aqua(Water),Sorbitol, Hydrated Silica, Xylitol,Glycerin, Aroma(Flavour), Disodium Phosphate.Sodium Lauroyl Sarcosinate, CalciumGlycerophosphate, Cellulose Gum, XanthanGum, Tetrapotassium Pyrophosphate.Benzyl Alcohol, Caprylyl Glycol, Sucralose, Menthol.Pentylene Glycol, Zinc Lactate, MethylDiisopropyl Propionamide, Benzoic Acid

Keep Oot Of Reach Of Children

Please place it out of the reach of children